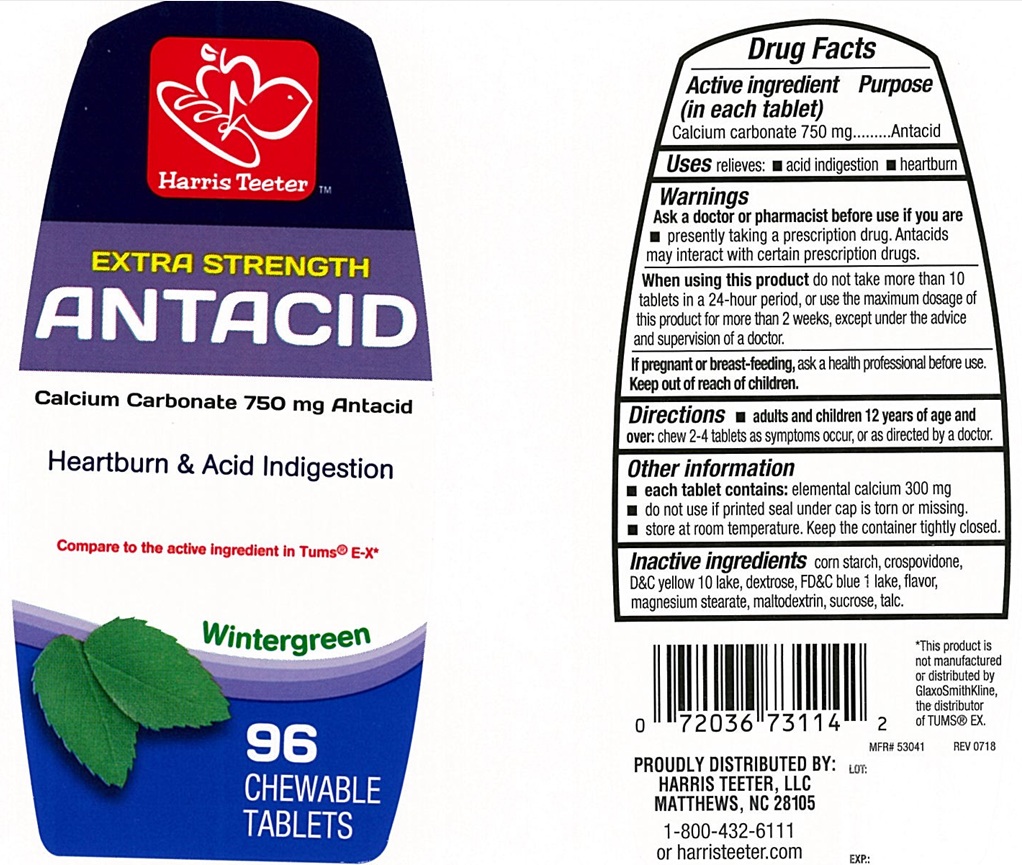 DRUG LABEL: Extra Strength Antacid
NDC: 69256-130 | Form: TABLET, CHEWABLE
Manufacturer: Harris Teeter, LLC
Category: otc | Type: Human OTC Drug Label
Date: 20250220

ACTIVE INGREDIENTS: CALCIUM CARBONATE 750 mg/1 1
INACTIVE INGREDIENTS: STARCH, CORN; DEXTROSE, UNSPECIFIED FORM; FD&C BLUE NO. 1 ALUMINUM LAKE; MAGNESIUM STEARATE; MALTODEXTRIN; SUCROSE; TALC; D&C YELLOW NO. 10 ALUMINUM LAKE; CROSPOVIDONE

Extra Strength Alkums Antacid Wintergreen Chewable Tablets

ACTIVE INGREDIENT (in each tablet)

Calcium carbonate 750 mg

PURPOSE

Antacid

USE(S)

relieves:

- acid indigestion
- heartburn

WARNINGS

.

ASK A DOCTOR OR PHARMACIST BEFORE USE IF YOU ARE

- presently taking a prescription drug. Antacids may interact with certain prescription drugs.

WHEN USING THIS PRODUCT

do not take more than 10 tablets in a 24-hour period, or use the maximum dosage of this product for more than 2 weeks, except under the advice and supervision of a doctor.

IF PREGNANT OR/BREASTFEEDING,

ask a health professional before use.

KEEP OUT OF REACH OF CHILDREN

.

DIRECTIONS

- adults and children 12 years of age and over: chew 2-4 tablets as symptoms occur, or as directed by a doctor.

OTHER INFORMATION

- each tablet contains: elemental calcium 300 mg
- do not use if printed seal under the cap is torn or missing
- store at room temperature. keep the container tightly closed.

INACTIVE INGREDIENTS

corn starch, crospovidone, D&C yellow 10 lake, dextrose, FD&C blue 1 lake, flavor, magnesium stearate, maltodextrin, sucrose, talc.

PRINCIPAL DISPLAY PANEL

Harris Teeter™

NDC 69256-130-22

EXTRA STRENGTH

ANTACID

Calcium Carbonate 750 mg Antacid

Heartburn & Acid Indigestion

Compare to the active ingredient in Tums® E-X*

Wintergreen

96 CHEWABLE TABLETS